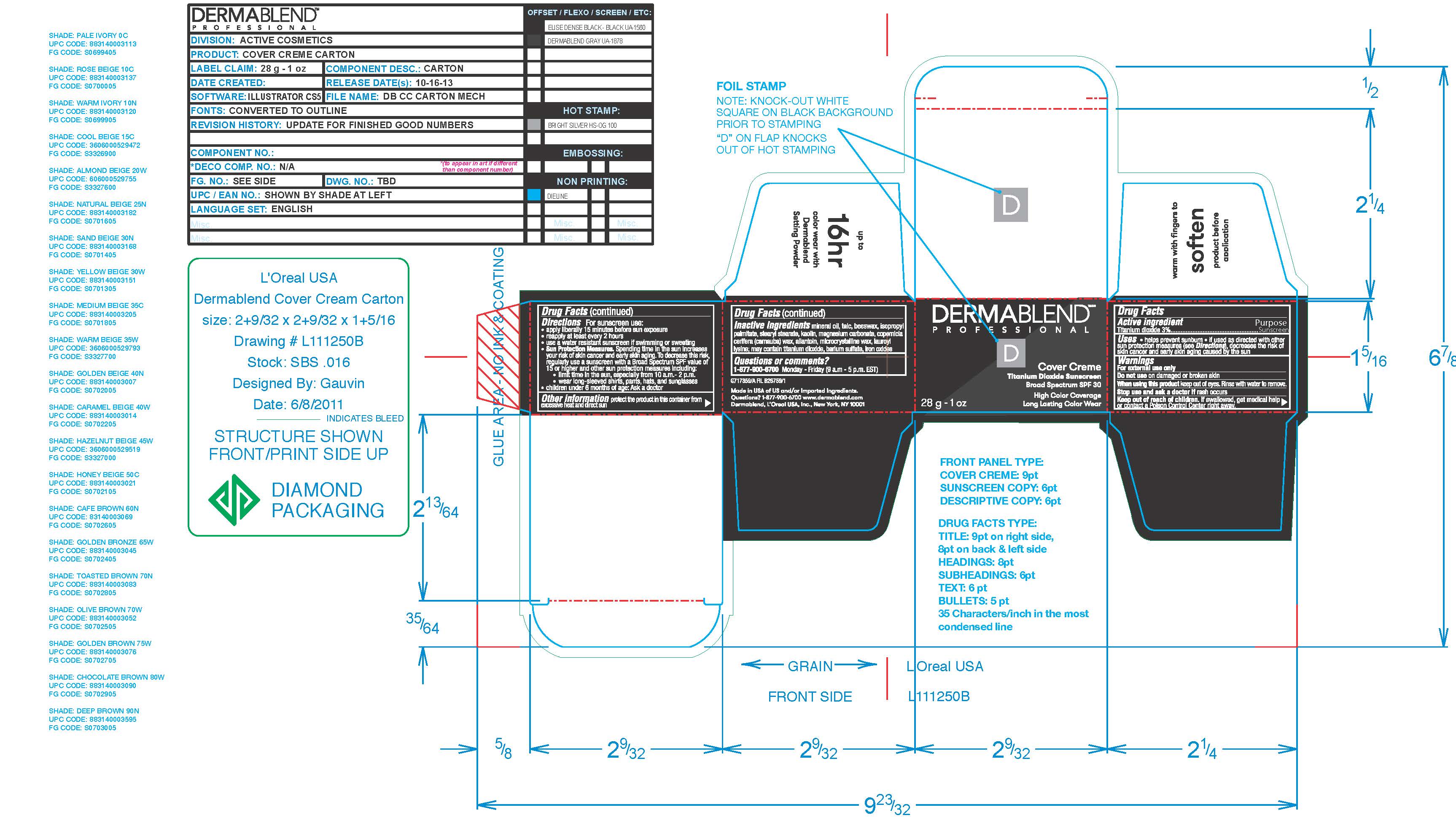 DRUG LABEL: Continuous Correction Cream
NDC: 84203-004 | Form: CREAM
Manufacturer: Baxter of California, LLC
Category: otc | Type: HUMAN OTC DRUG LABEL
Date: 20250724

ACTIVE INGREDIENTS: TITANIUM DIOXIDE 30 mg/1 g
INACTIVE INGREDIENTS: MINERAL OIL; TALC

Dermablend Professional CC Cream SPF 30

Active Ingredient

Titanium Dioxide 3%

Purpose

Sunscreen

Uses

helps prevent sunburn

if used as directed with other sun protection measures (see Directions), decreases the risk of skin cancer and early skin aging caused by the sun.

Warnings

For external use only

Do not use on damaged or broken skin

When using this product keep out of eyes. Rinse with water to remove.

Stop use and ask a doctor if rash occurs

Keep out of reach of children. If swallowed, get medical help or contact a Poison Control Center right away.

Directions

For sunscreen use:

-apply liberally 15 minutes before sun exposure

-reapply at least every 2 hours\

-use a water resistant sunscreen if swimming or sweating

-Sun Protection Measures. Spending time in the sun increase your risk of skin cancer and early skin aging. To decrease this risk, regularly use sun screen with a Broad Spectrum SPF value of 15 or higher and other sun protection measures including:

-limit time in the sun, especially from 10am-2pm

-wear long-sleeved shirts, pants, hats and sunglasses

Children under 6 months of age: Ask a doctor

Other information

protect the product in this container from excessive heat and direct sun

Inactive ingredients

mineral oil, talc, beeswax, isopropyl palmitate, stearyl stearate, kaolin, magnesium carbonate, copernicia cerifera (carnauba) wax, allantoin, microcrystalline wax, lauroyl lysine; may contain titanium dioxide, barium sulfate, iron oxides

Questions or comments?

1-877-900-6700 Monday-Friday (9am-5pm EST)